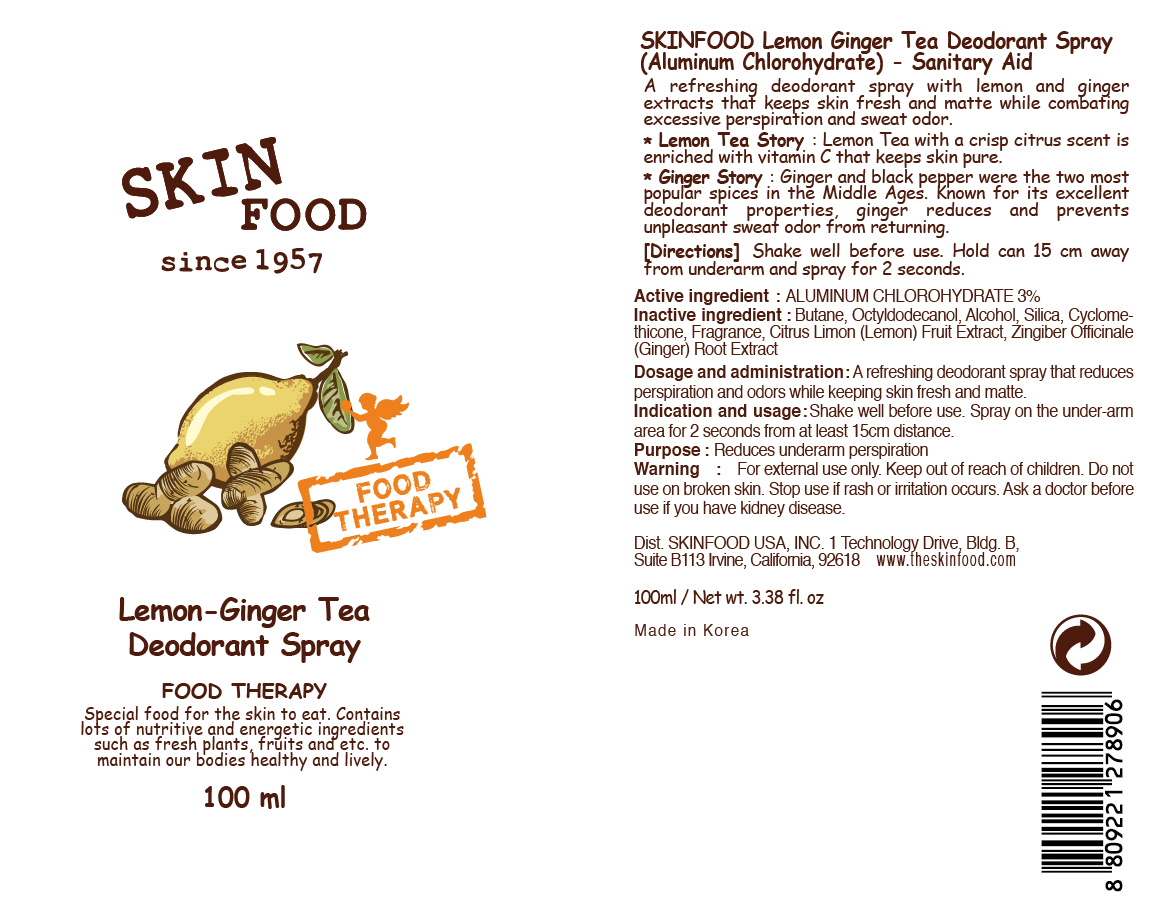 DRUG LABEL: LEMON GINGER TEA DEODORANT
NDC: 76214-009 | Form: SPRAY
Manufacturer: SKINFOOD CO., LTD.
Category: otc | Type: HUMAN OTC DRUG LABEL
Date: 20110721

ACTIVE INGREDIENTS: ALUMINUM CHLOROHYDRATE 3 mL/100 mL
INACTIVE INGREDIENTS: BUTANE; OCTYLDODECANOL; ALCOHOL; SILICON DIOXIDE; CYCLOMETHICONE; CITRUS LIMON FRUIT OIL; GINGER

Drug Facts

Active ingredient: ALUMINUM CHLOROHYDRATE

Inactive ingredients:

Butane, Octyldodecanol, Alcohol, Silica, Cyclomethicone, Fragrance, Citrus Limon (Lemon) Fruit Extract, Zingiber Officinale (Ginger) Root Extract

Purpose:

Reduces underarm perspiration.

Warnings:

For external use only.
Do not use on broken skin. Stop use if rash or irritation occurs.
Ask a doctor before use if you have kidney disease.

Keep out of reach of children:

Keep out of reach of children.

Indication and usage:

Shake well before use. Spray on the under-arm area for 2 seconds from at least 15cm distance.

Dosage and administration:

A refreshing deodorant spray that reduces perspiration and odors while keeping skin fresh and matte.